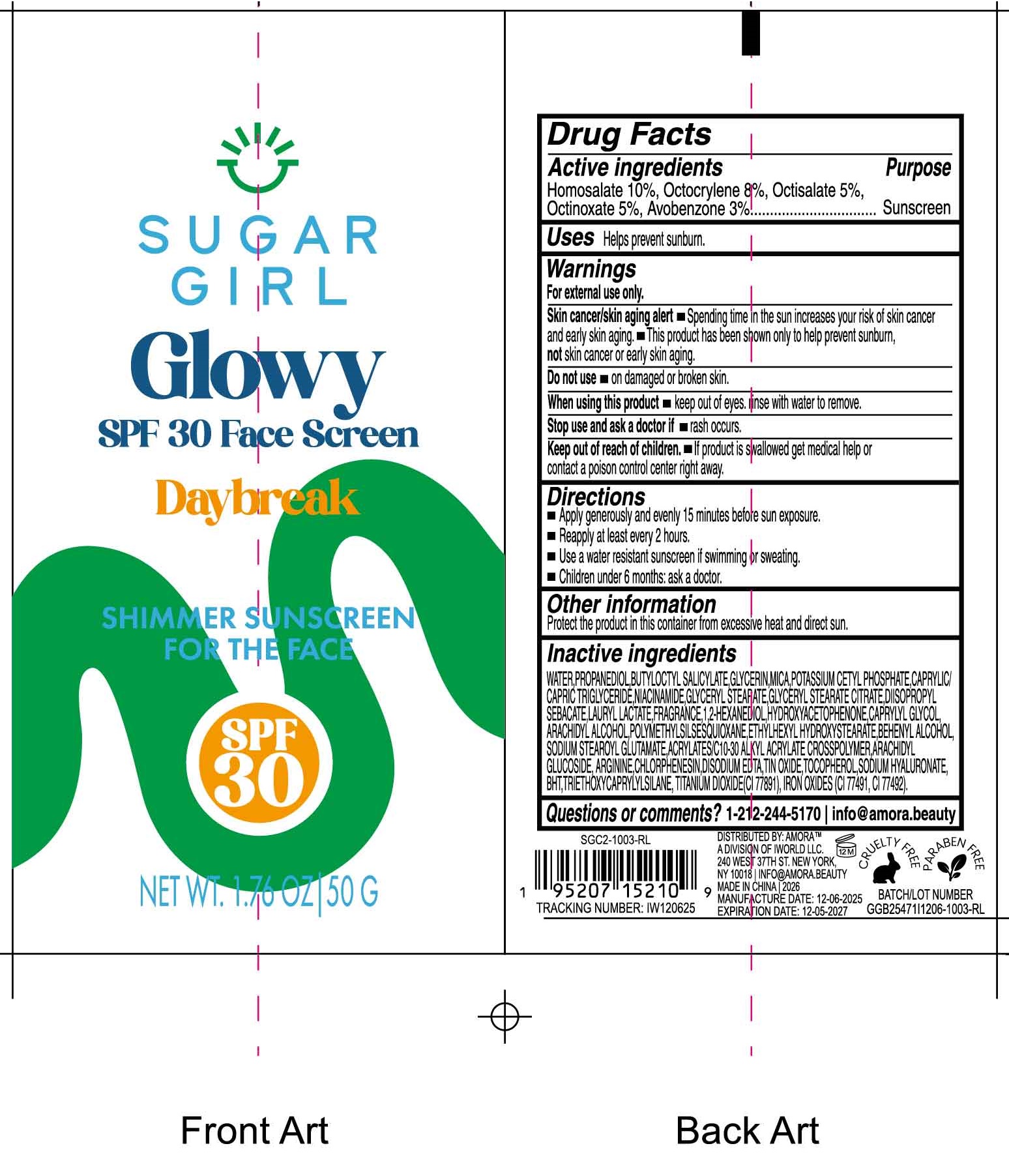 DRUG LABEL: Sugargirl Glowy SPF 30 Face Screen Daybreak Shimmer Sunscreen For the Face
NDC: 85179-030 | Form: LIQUID
Manufacturer: I World LLC
Category: otc | Type: HUMAN OTC DRUG LABEL
Date: 20260109

ACTIVE INGREDIENTS: HOMOSALATE 100 mg/1 g; OCTOCRYLENE 80 mg/1 g; OCTISALATE 50 mg/1 g; OCTINOXATE 50 mg/1 g; AVOBENZONE 30 mg/1 g
INACTIVE INGREDIENTS: WATER; PROPANEDIOL; BUTYLOCTYL SALICYLATE; GLYCERIN; MICA; POTASSIUM CETYL PHOSPHATE; MEDIUM-CHAIN TRIGLYCERIDES; NIACINAMIDE; GLYCERYL MONOSTEARATE; GLYCERYL STEARATE CITRATE; DIISOPROPYL SEBACATE; LAURYL LACTATE; 1,2-HEXANEDIOL; HYDROXYACETOPHENONE; CAPRYLYL GLYCOL; ARACHIDYL ALCOHOL; ETHYLHEXYL HYDROXYSTEARATE; BEHENYL ALCOHOL; SODIUM STEAROYL GLUTAMATE; ARACHIDYL GLUCOSIDE; ARGININE; CHLORPHENESIN; EDETATE DISODIUM; STANNIC OXIDE; TOCOPHEROL; SODIUM HYALURONATE; BUTYLATED HYDROXYTOLUENE; TRIETHOXYCAPRYLYLSILANE; TITANIUM DIOXIDE; FERRIC OXIDE RED; FERRIC OXIDE YELLOW

Sugargirl Glowy SPF 30 Face Screen Daybreak Shimmer Sunscreen For the Face

Active ingredients

Homosalate 10%, Octocrylene 8%, Octisalate 5%, Octinoxate 5%, Avobenzone 3%

Purpose

Sunscreen

Uses

Helps prevent sunburn.

Warnings

For external use only.

Skin cancer/skin aging alert

- Spending time in the sun increases your risk of skin cancer and early skin aging.
- This product has been shown only to help prevent sunburn, not skin cancer or early skin aging.

Do not use

- on damaged or broken skin.

When using this product

- keep out of eyes. rinse with water to remove.

Stop use and ask doctor if

- rash occurs.

Keep out of reach of children.

- If product is swallowed get medical help or contact a poison control center right away.

Directions

- Apply generously and evenly 15 minutes before sun exposure.
- Reapply at least every 2 hours
- Use a water resistant sunscreen if swimming or sweating.
- Children under 6 month: ask a doctor.

Other information

Protect the product in this container from excessive heat and direct sun.

Inactive ingredients

WATER, PROPANEDIOL, BUTYLOCTYL SALICYLATE, GLYCERIN, MICA, POTASSIUM CETYL PHOSPHATE, CAPRYLIC/CAPRIC TRIGLYCERIDE, NIACINAMIDE, GLYCERYL STEARATE, GLYCERYL STEARATE CITRATE, DIISOPROPYL SEBACATE, LAURYL LACTATE, FRAGRANCE, 1,2-HEXANEDIOL, HYDROXYACETOPHENONE, CAPRYLYL GLYCOL, ARACHIDYL ALCOHOL, POLYMETHYLSILSEQUIOXANE, ETHYLHEXYL HYDROXYSTEARATE, BEHENYL ALCOHOL, SODIUM STEAROYL GLUTAMATE, ACRYLATES/C 10-30 ALKYL ACRYLATE CROSSPOLYMER, ARACHIDYL GLUCOSIDE, ARGININE, CHLORPHENESIN, DISODIUM EDTA, TIN OXIDE, TOCOPHEROL, SODIUM HYALURONATE, BHT, TRIETHOXYCAPRYLYLSILANE, TITANIUM DIOXIDE (CI 77891), IRON OXIDES (CI 77491, CI 77492).

Questions or comments?

1-212- 244-5170 info@amora.beauty